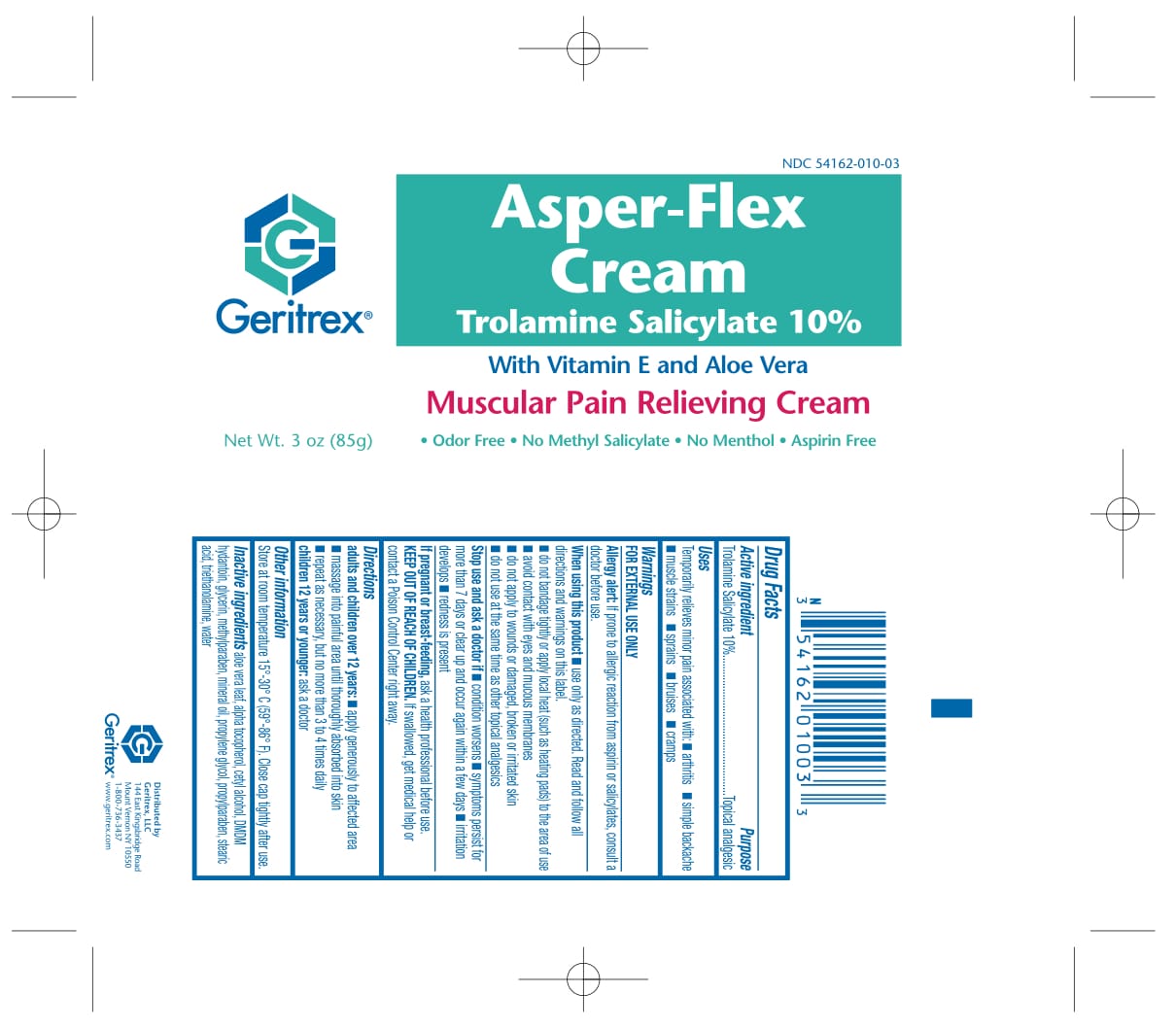 DRUG LABEL: Asper-Flex 
NDC: 54162-010 | Form: CREAM
Manufacturer: Geritrex LLC
Category: otc | Type: HUMAN OTC DRUG LABEL
Date: 20170911

ACTIVE INGREDIENTS: Trolamine Salicylate 8.5 g/85 g
INACTIVE INGREDIENTS: ALOE VERA LEAF; .ALPHA.-TOCOPHEROL; CETYL ALCOHOL; GLYCERIN; DMDM HYDANTOIN; METHYLPARABEN; MINERAL OIL; PROPYLPARABEN; STEARIC ACID; TROLAMINE; WATER

Asper-Flex Cream

Drug Facts

Active Ingredients...................................Purpose
Trolamine Salicylate(10%).......................Topical Analgesic

Uses

For the temporary relief of minor aches and pains of
muscles and joints associated with arthritis, simple backaches,
strains and sprains.

Directions

Apply generously to affected area. Massage
into painful area until thoroughly absorbed into skin.
Repeat as necessary, but not more than 4 times daily.

DOSAGE AND ADMINISTRATION

No more than 4 times daily.

Warnings

• Use only as directed • If prone to allergic
reaction from aspirin or salicylate, consult a doctor • If redness
is present, discontinue use and consult a doctor • If
condition worsens or if pain persists for more than 7 days
or clears up and occurs again within a few days, discontinue
use and consult a doctor • Avoid contact with eyes • As
with any drug, if you are pregnant or nursing a baby, seek
the advice of a health professional before using this product
Do not use: • On children under 10 years of age • If
skin is irritated or if irritation develops • KEEP THIS AND
ALL MEDICINE OUT OF THE REACH OF CHILDREN • In
case of accidental ingestion, seek professional assistance or
contact a poison control center immediately

Other Ingredients

Aloe Vera Gel, Alpha Tocopherol, Cetyl Alcohol, Glycerin, DMDM Hydantoin, Methylparaben, Mineral Oil, Propylene Glycol, Propylparaben, Stearic Acid, Triethanolamine, Water

Storage

At room temperature 15º-30º C (59º-86º F).
Close cap tightly after use.

Keep out of reach of children

KEEP THIS AND ALL MEDICINE OUT OF THE REACH OF CHILDREN